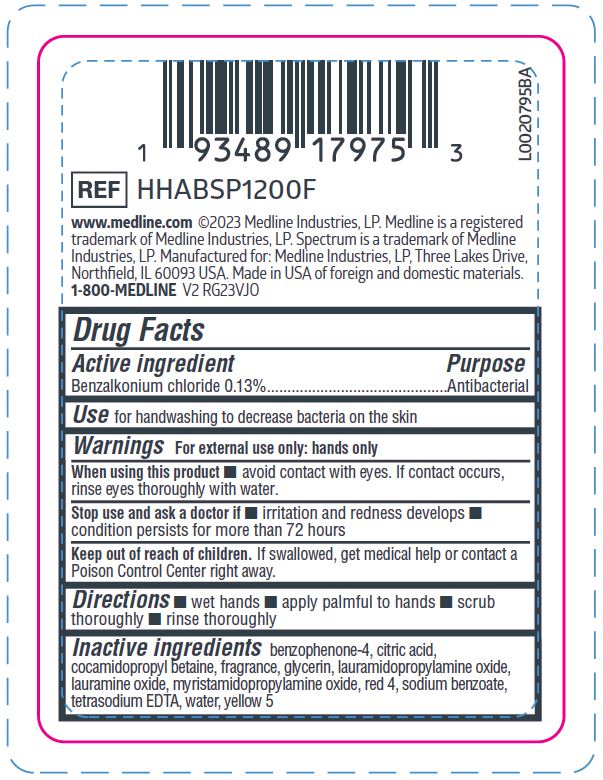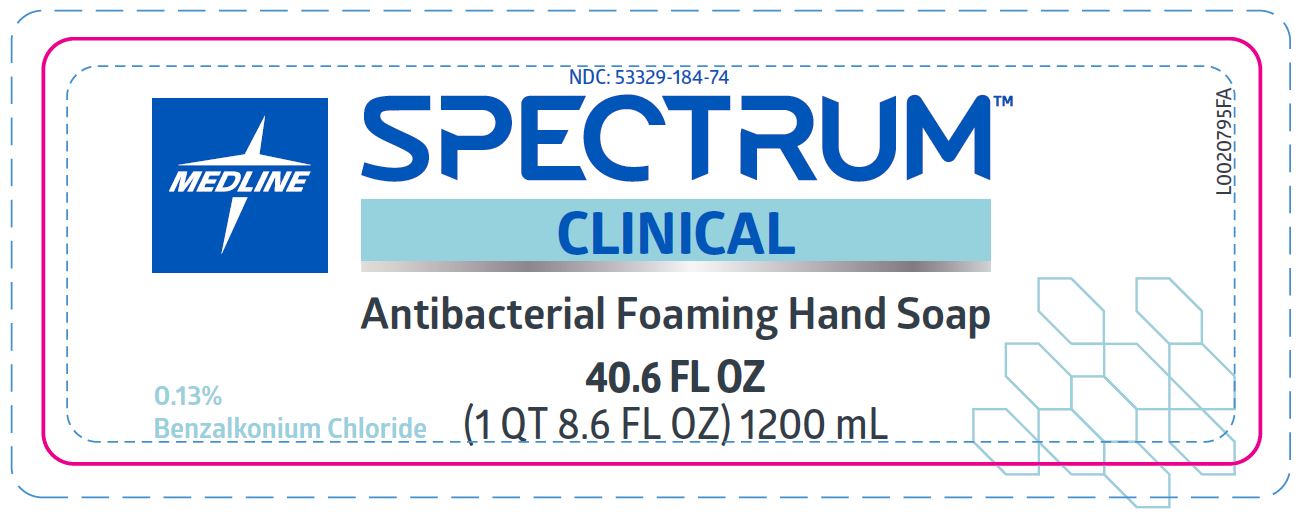 DRUG LABEL: Cleanse
NDC: 53329-184 | Form: SOLUTION
Manufacturer: Medline Industries, LP
Category: otc | Type: HUMAN OTC DRUG LABEL
Date: 20260211

ACTIVE INGREDIENTS: BENZALKONIUM CHLORIDE 0.13 g/100 mL
INACTIVE INGREDIENTS: WATER; LAURAMINE OXIDE; EDETATE SODIUM; GLYCERIN; ANHYDROUS CITRIC ACID; FD&C YELLOW NO. 5; COCAMIDOPROPYL BETAINE; FD&C RED NO. 4; SULISOBENZONE; MYRISTAMIDOPROPYLAMINE OXIDE; LAURAMIDOPROPYLAMINE OXIDE; SODIUM BENZOATE

184 Antibacterial Foaming Hand Soap

Active ingredient

Benzalkonium chloride 0.13%

Purpose

Antibacterial

Use

for handwashing to decrease bacteria on the skin

Warnings

For external use only: hands only

When using this product

- avoid contact with the eyes. If contact occurs, rinse eyes thoroughly with water.

Stop use and ask a doctor if

- irritation and redness develops
- condition persists for more than 72 hours

Keep out of reach of children.

If swallowed, get medical help or contact a Poison Control Center right away.

Directions

- wet hands
- apply palmful to hands
- scrub thoroughly
- rinse thoroughly

Inactive ingredients

benzophenone-4, citric acid, cocamidopropyl betaine, fragrance, glycerin, lauramidopropylamine oxide, lauramine oxide, myristamidopropylamine oxide, red 4, sodium benzoate, tetrasodium EDTA, water, yellow 5

Manufacturing Information

www.medline.com

©2022 Medline Industries, LP.

Medline is a registered trademark of Medline Industries, LP.

Spectrum is a trademark of Medline Industries, LP.

Made in USA of foreign and domestic materials

Manufactured for Medline Industries, LP

Three Lakes Drive, Northfield, IL 60093 USA

1-800-MEDLINE

REF: HHABSP1200F